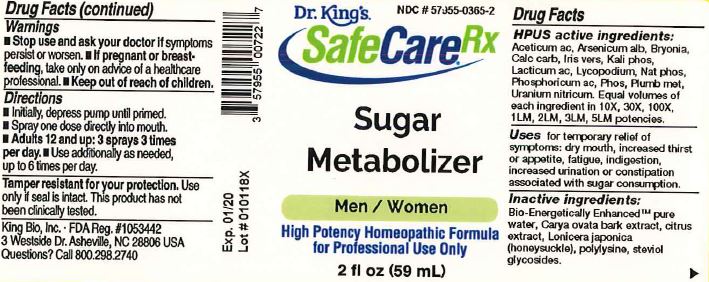 DRUG LABEL: Sugar Metabolizer
NDC: 57955-0365 | Form: LIQUID
Manufacturer: King Bio Inc.
Category: homeopathic | Type: HUMAN OTC DRUG LABEL
Date: 20180329

ACTIVE INGREDIENTS: ACETIC ACID 10 [hp_X]/59 mL; ARSENIC TRIOXIDE 10 [hp_X]/59 mL; BRYONIA ALBA ROOT 10 [hp_X]/59 mL; OYSTER SHELL CALCIUM CARBONATE, CRUDE 10 [hp_X]/59 mL; IRIS VERSICOLOR ROOT 10 [hp_X]/59 mL; POTASSIUM PHOSPHATE, DIBASIC 10 [hp_X]/59 mL; LACTIC ACID, DL- 10 [hp_X]/59 mL; LYCOPODIUM CLAVATUM SPORE 10 [hp_X]/59 mL; SODIUM PHOSPHATE, DIBASIC, HEPTAHYDRATE 10 [hp_X]/59 mL; PHOSPHORIC ACID 10 [hp_X]/59 mL; PHOSPHORUS 10 [hp_X]/59 mL; LEAD 10 [hp_X]/59 mL; URANYL NITRATE HEXAHYDRATE 10 [hp_X]/59 mL
INACTIVE INGREDIENTS: WATER; CARYA OVATA BARK; CITRUS BIOFLAVONOIDS; LONICERA JAPONICA FLOWER; POLYEPSILON-LYSINE (4000 MW); REBAUDIOSIDE A

Sugar Metabolizer

ACTIVE INGREDIENT

Drug Facts__________________________________________________________________________________________________________

HPUS active ingredients: Aceticum acidum, Arsenicum album, Bryonia, Calcarea carbonica, Iris versicolor, Kali phosphoricum, Lacticum acidum, Lycopodium clavatum, Natrum phosphoricum, Phosphoricum acidum, Phosphorus, Plumbum metallicum, Uranium nitricum. Equal volumes of each ingredient in 10X, 30X, 100X, 1LM, 2LM, 3LM, 5LM potencies.

INDICATIONS AND USAGE

Uses for temporary relief of symptoms: dry mouth, increased thirst or appetite, fatigue, indigestion, increased urination or constipation associated with sugar consumption.

Inactive Ingredients:

Bio-Energetically Enhanced™ pure water, Carya ovata bark extract, citrus exract, Lonicera japonica (honesuckle), polylysine, steviol glycosides.

Warnings

- Stop use and ask your doctor if symptoms persist or worsen.
- If pregnant or breast-feeding, take only on advice of a healthcare professional.

- Keep out of reach of children.

Directions

- Initially, depress pump until primed.
- Spray one dose directly into mouth.
- Adults 12 and up: 3 sprays 3 times per day
- Use additionally as needed, up to 6 times per day.

OTHER SAFETY INFORMATION

Tamper resistant for your protection. Use only if safety seal is intact. This product has not been clinically tested.

PURPOSE

Uses for temporary relief of symptoms:

- dry mouth
- increased thirst or appetite
- fatigue
- indigestion
- increased urination or constipation associated with sugar consumption